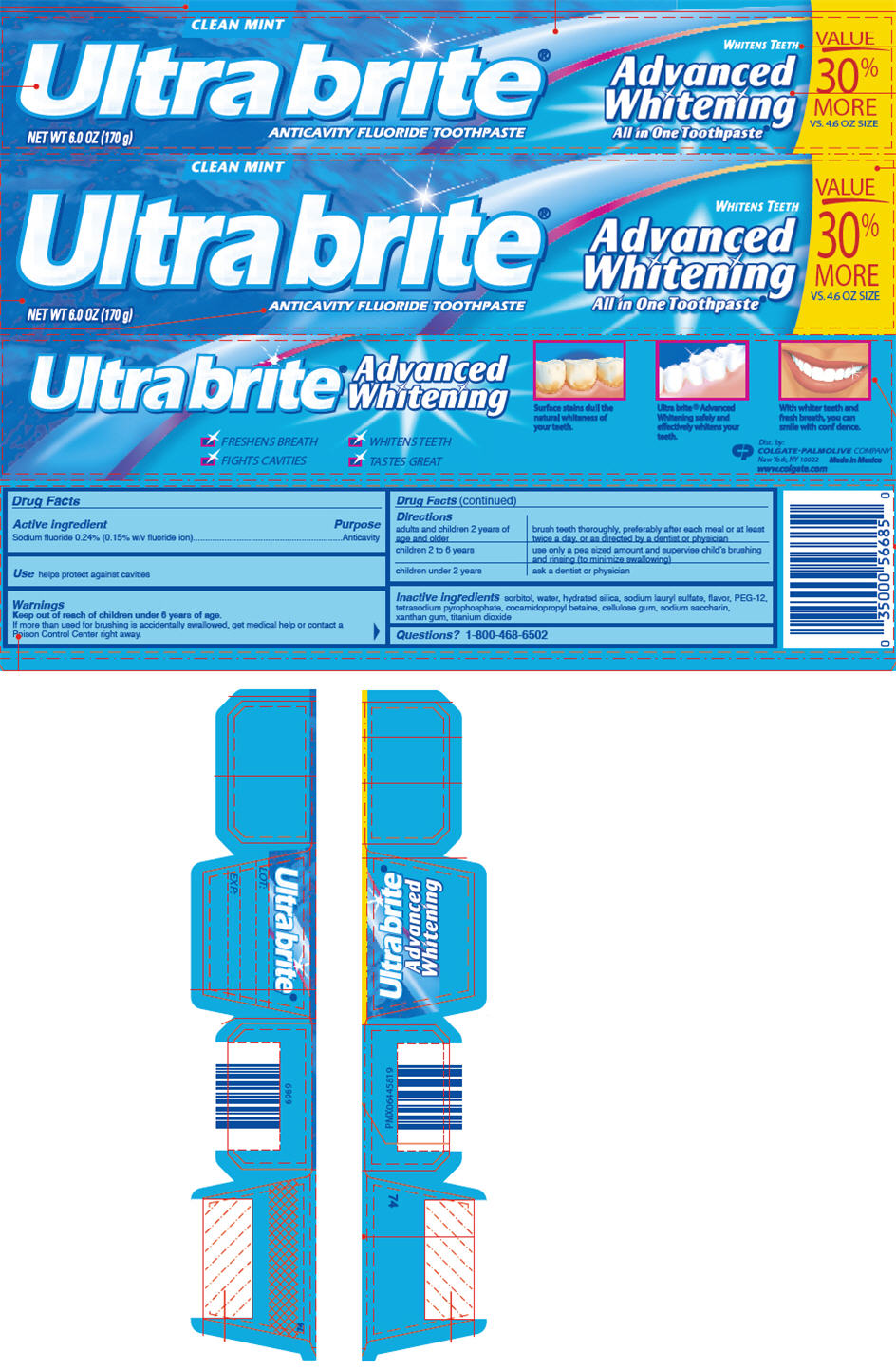 DRUG LABEL: COLGATE ULTRA BRITE ADVANCED WHITENING ALL IN ONE CLEAN MINT
NDC: 35000-917 | Form: PASTE, DENTIFRICE
Manufacturer: Colgate-Palmolive Company
Category: otc | Type: HUMAN OTC DRUG LABEL
Date: 20191204

ACTIVE INGREDIENTS: SODIUM FLUORIDE 1.1 mg/1 g
INACTIVE INGREDIENTS: SORBITOL 630.33 mg/1 g; WATER; HYDRATED SILICA; SODIUM LAURYL SULFATE; POLYETHYLENE GLYCOL 600; SODIUM PYROPHOSPHATE; COCAMIDOPROPYL BETAINE; CARBOXYMETHYLCELLULOSE SODIUM, UNSPECIFIED; SACCHARIN SODIUM; XANTHAN GUM; TITANIUM DIOXIDE

COLGATE ULTRA BRITE® ADVANCED WHITENING ALL IN ONE CLEAN MINT

Drug Facts

Active ingredient

Sodium fluoride 0.24% (0.15% w/v fluoride ion)

Purpose

Anticavity

Use

helps protect against cavities

Warnings

Keep out of reach of children under 6 years of age.

If more than used for brushing is accidentally swallowed, get medical help or contact a Poison Control Center right away.

Directions

adults and children 2 years of age and older | brush teeth thoroughly, preferably after each meal or at least twice a day, or as directed by a dentist or physician
children 2 to 6 years | use only a pea sized amount and supervise child's brushing and rinsing (to minimize swallowing)
children under 2 years | ask a dentist or physician

Inactive ingredients

sorbitol, water, hydrated silica, sodium lauryl sulfate, flavor, PEG-12, tetrasodium pyrophosphate, cocamidopropyl betaine, cellulose gum, sodium saccharin, xanthan gum, titanium dioxide

Questions?

1-800-468-6502

Dist. by:
COLGATE-PALMOLIVE COMPANY
New York, NY 10022

PRINCIPAL DISPLAY PANEL - 170 g Tube Carton

CLEAN MINT

Ultra brite®

ANTICAVITY FLUORIDE TOOTHPASTE

WHITENS TEETH

Advanced
Whitening
All in One Toothpaste®

VALUE
30%
MORE
VS. 4.6 OZ SIZE

NET WT 6.0 OZ (170 g)